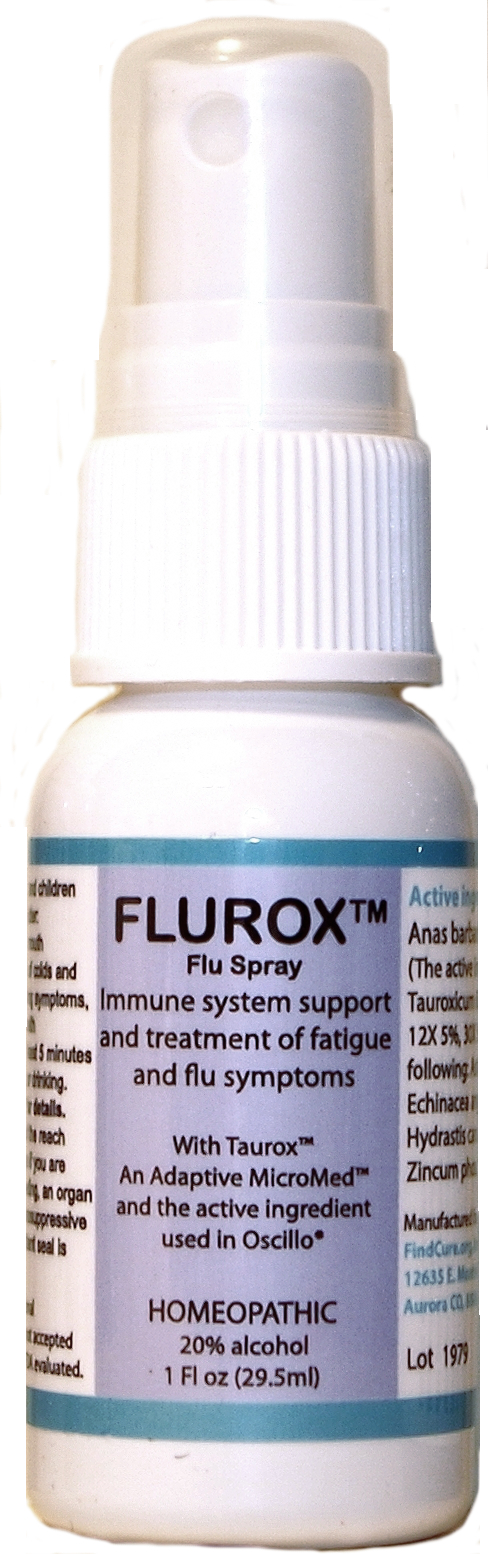 DRUG LABEL: Flurox Flu
NDC: 73311-005 | Form: LIQUID
Manufacturer: CureImmune Corp.
Category: homeopathic | Type: HUMAN OTC DRUG LABEL
Date: 20190826

ACTIVE INGREDIENTS: ASTRAGALUS NUTTALLII LEAF 6 [hp_X]/1 1; GOLDENSEAL 6 [hp_X]/1 1; ZINC CARBOBENZOXY-.BETA.-ALANYLTAURINATE 6 [hp_X]/1 1; ECHINACEA ANGUSTIFOLIA 6 [hp_X]/1 1; ZINC PHOSPHATE 12 [hp_X]/1 1; CAIRINA MOSCHATA HEART/LIVER AUTOLYSATE 200 [hp_M]/1 1
INACTIVE INGREDIENTS: WATER; ALCOHOL

Flurox Flu Spray

Active Ingredients

Anas Barbariae 200CK 61.7%;

Tauroxicum 6X 5.8%

2.5% for each of the following:

Astragalus 6X, 12X, 30X

Echinacea ang 6X, 12X, 30X

Hydrastis 6X, 12X, 30X

Tauroxicum 12X, 30X

Zinc phos, 12X, 30X

Use

Immune system support and treatment of fatigue and flu symptoms

PURPOSE

Immune system support and treatment of fatigue and flu symptoms

Directions

Directions for adults and children 15 years of age and older: Take 2 to 4 sprays in mouth weekly for prevention of colds and flu, and take daily during symptoms, or as directed by a health professional. Take at least 5 minutes before or after eating or drinking. See package insert for details.

Warnings

Keep out of reach of children. Do not use if you are pregnant or breast feeding, an organ recipient, using immunosuppressive drugs, or if the tamper-evident seal is broken or missing. See package insert for details.

Keep out of reach of children.

Inactive Ingredients

20% alcohol (ethanol), purified water

Disclaimer

Claims based on traditional
homeopathic practice, not accepted
medical evidence. Not FDA evaluated.

PACKAGE LABEL

Flurox

Flu Spray

Immune system support

and treatment of fatigue

and flu symptoms

With Taurox

An Adaptive MicroMed

and the active ingredient

used in Oscillo®

HOMEOPATHIC

20% alcohol

1 Fl oz (29.5ml)